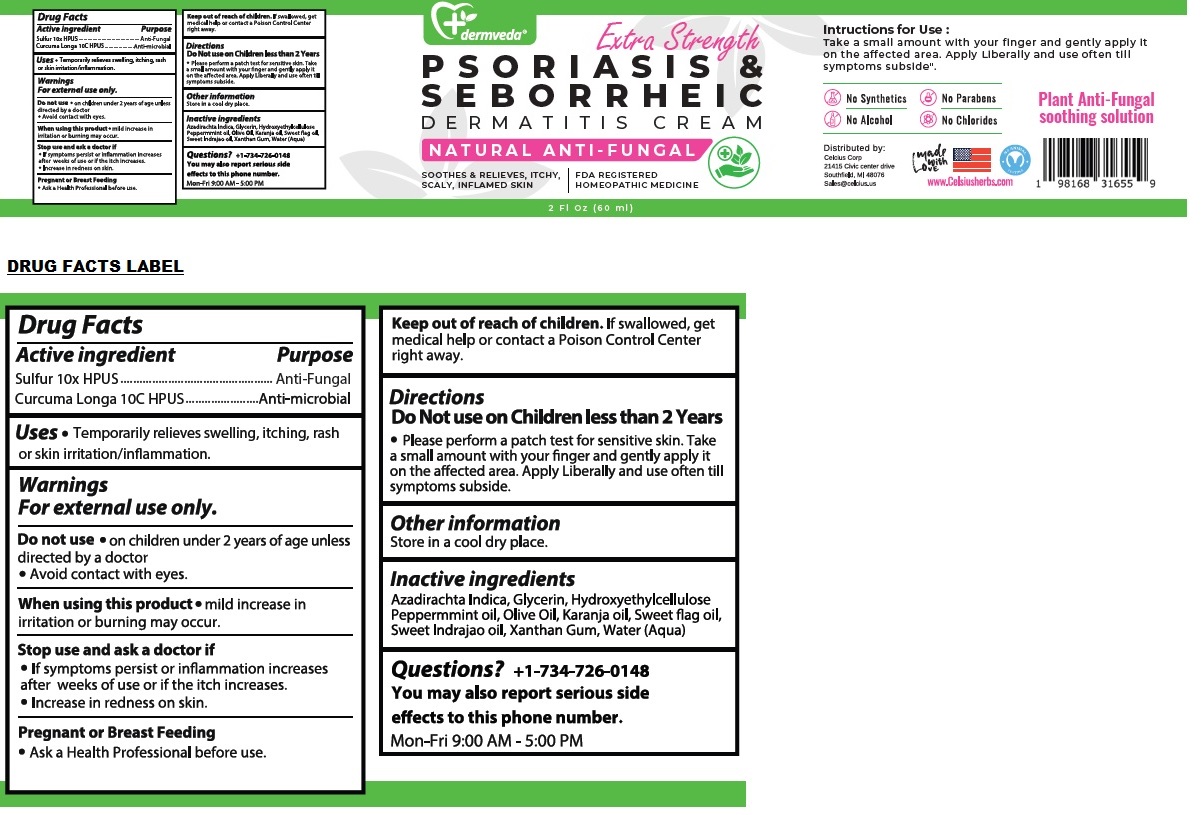 DRUG LABEL: dermveda PSORIASIS AND SEBORRHEIC DERMATITIS
NDC: 83819-306 | Form: CREAM
Manufacturer: Celcius Corp.
Category: homeopathic | Type: HUMAN OTC DRUG LABEL
Date: 20260209

ACTIVE INGREDIENTS: SULFUR 10 [hp_X]/60 mL; CURCUMA LONGA WHOLE 10 [hp_C]/60 mL
INACTIVE INGREDIENTS: AZADIRACHTA INDICA BARK; GLYCERIN; HYDROXYETHYL CELLULOSE, UNSPECIFIED; PEPPERMINT OIL; OLIVE OIL; KARUM SEED OIL; CALAMUS OIL; WRIGHTIA TINCTORIA WHOLE; XANTHAN GUM; WATER

dermveda™ PSORIASIS & SEBORRHEIC DERMATITIS CREAM

Active ingredient

Sulfur 10x HPUS
Curcuma Longa 10C HPUS

Purpose

Anti-Fungal
Anti-microbial

Uses

• Temporarily relieves swelling, itching, rash or skin irritation/inflammation.

Warnings

For external use only.

Do not use • on children under 2 years of age unless directed by a doctor
• Avoid contact with eyes.

When using this product • mild increase in irritation or burning may occur.

Stop use and ask a doctor if
• If symptoms persist or inflammation increases after weeks of use or if the itch increases.
• Increase in redness on skin.

Pregnant or Breast Feeding
• Ask a Health Professional before use.

Keep out of reach of children. If swallowed, get medical help or contact a Poison Control Center right away.

Directions

Do Not use on Children less than 2 Years

• Please perform a patch test for sensitive skin. Take a small amount with your finger and gently apply it on the affected area. Apply Liberally and use often till symptoms subside.

Other information

Store in a cool dry place.

Inactive ingredients

Azadirachta Indica, Glycerin, Hydroxyethylcellulose, Peppermint oil, Olive Oil, Karanja oil, Sweet flag oil, Sweet Indrajao oil, Xanthan Gum, Water (Aqua)

Questions?

+1-734-726-0148
You may also report serious side effects to this phone number.
Mon-Fri 9:00 AM - 5:00 PM

Extra Strength

NATURAL ANTI-FUNGAL

SOOTHES & RELIEVES, ITCHY, SCALY, INFLAMED SKIN

FDA REGISTERED HOMEOPATHIC MEDICINE

No Synthetics

No Parabens

No Alcohol

No Chlorides

Plant Anti-Fungal soothing solution

Distributed by:
Celcius Corp
21415 Civic center drive
Southfield, MI 48076
Sales@celcius.us

made with Love

www.Celsiusherbs.com

NO ANIMAL TESTING